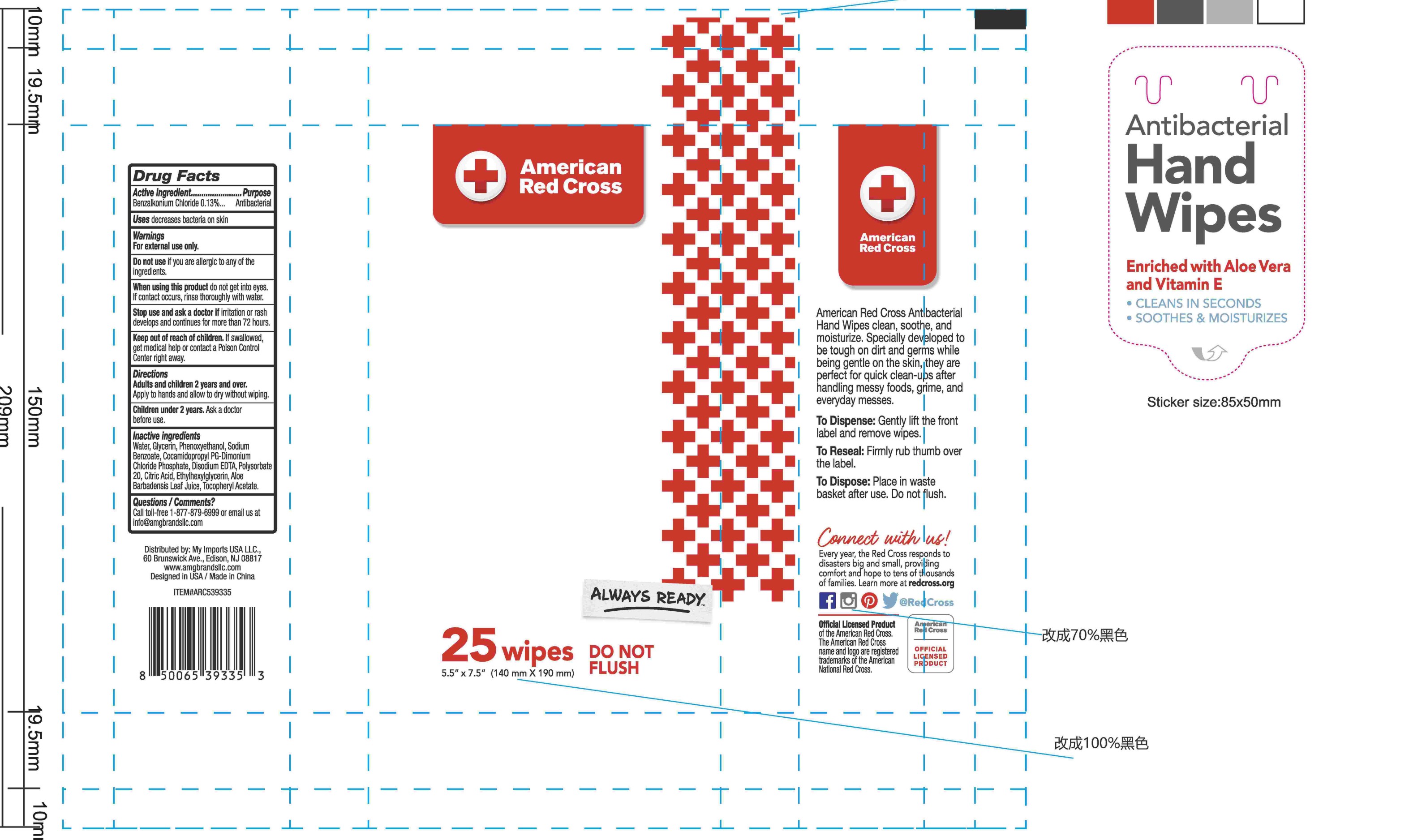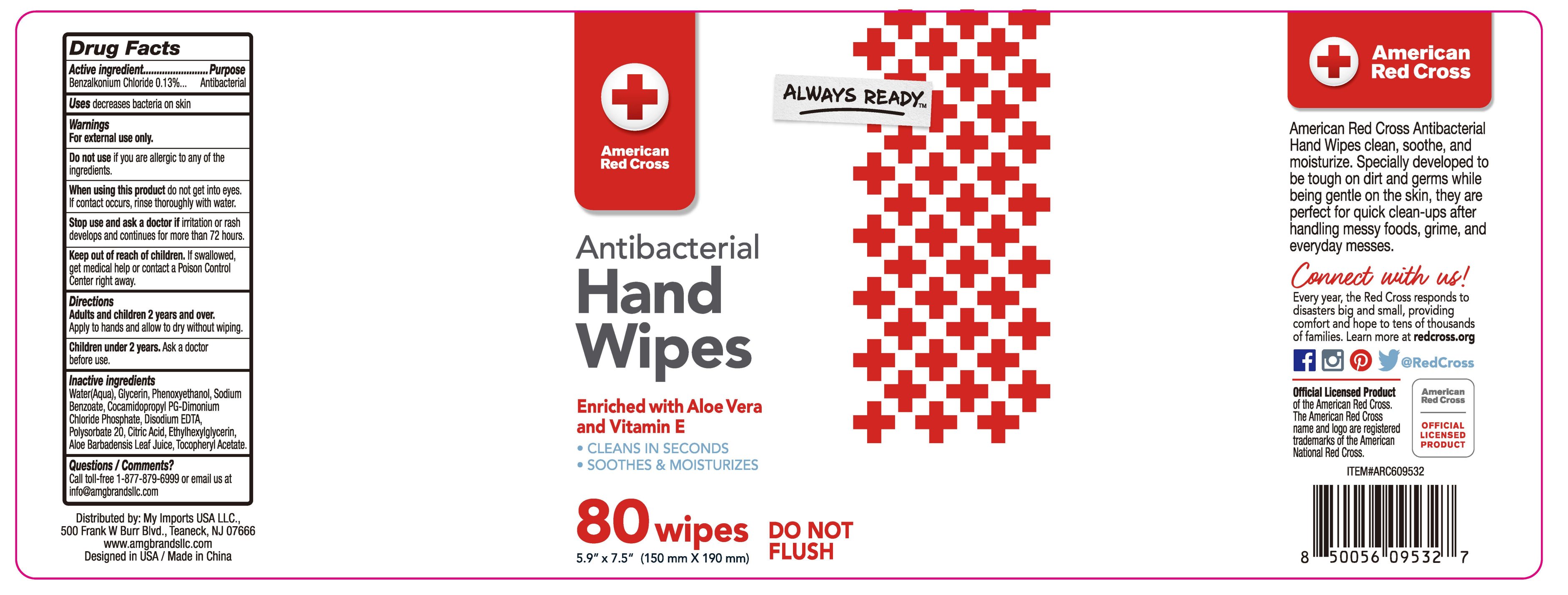 DRUG LABEL: Antibacterial Hand wipes
NDC: 51628-9999 | Form: CLOTH
Manufacturer: MY IMPORTS USA LLC
Category: otc | Type: HUMAN OTC DRUG LABEL
Date: 20250819

ACTIVE INGREDIENTS: BENZALKONIUM CHLORIDE 0.13 g/100 g
INACTIVE INGREDIENTS: COCAMIDOPROPYL PG-DIMONIUM CHLORIDE PHOSPHATE; DISODIUM EDTA-COPPER; WATER; GLYCERIN; SODIUM BENZOATE; ALOE BARBADENSIS LEAF; .ALPHA.-TOCOPHEROL ACETATE, D-; ETHYLHEXYLGLYCERIN; PHENOXYETHANOL; CITRIC ACID; POLYSORBATE 20

51628-9999

Active Ingredient

Benzalkonium Chloride 0.13%

Purpose

.Antibacterial

USE

decreases bacteria on skin

Warning

For external use only.
Do not use if you are allergic to any of theingredients.
When using this product do not get into eyes.
f contact occurs, rinse thoroughly with water.
Stop use and ask a doctor if irritation or rashdevelops and continues for more than 72 hours

Keep out of reach of children. lf swallowedget medical help or contact a Poison ControlCenter right away.

Directions

Adults and children 2 years and over.Apply to hands and allow to dry without wiping.
Children under 2 years. Ask a doctorbefore use.

Inactive ingredients

Water, Glycerin, Phenoxyethanol, SodiumBenzoate, Cocamidopropyl PG-DimoniumChloride Phosphate, Disodium EDTA, Polysorbate20, Citric Acid, Ethylhexylglycerin, AloeBarbadensis Leaf Juice, Tocopheryl Acetate.